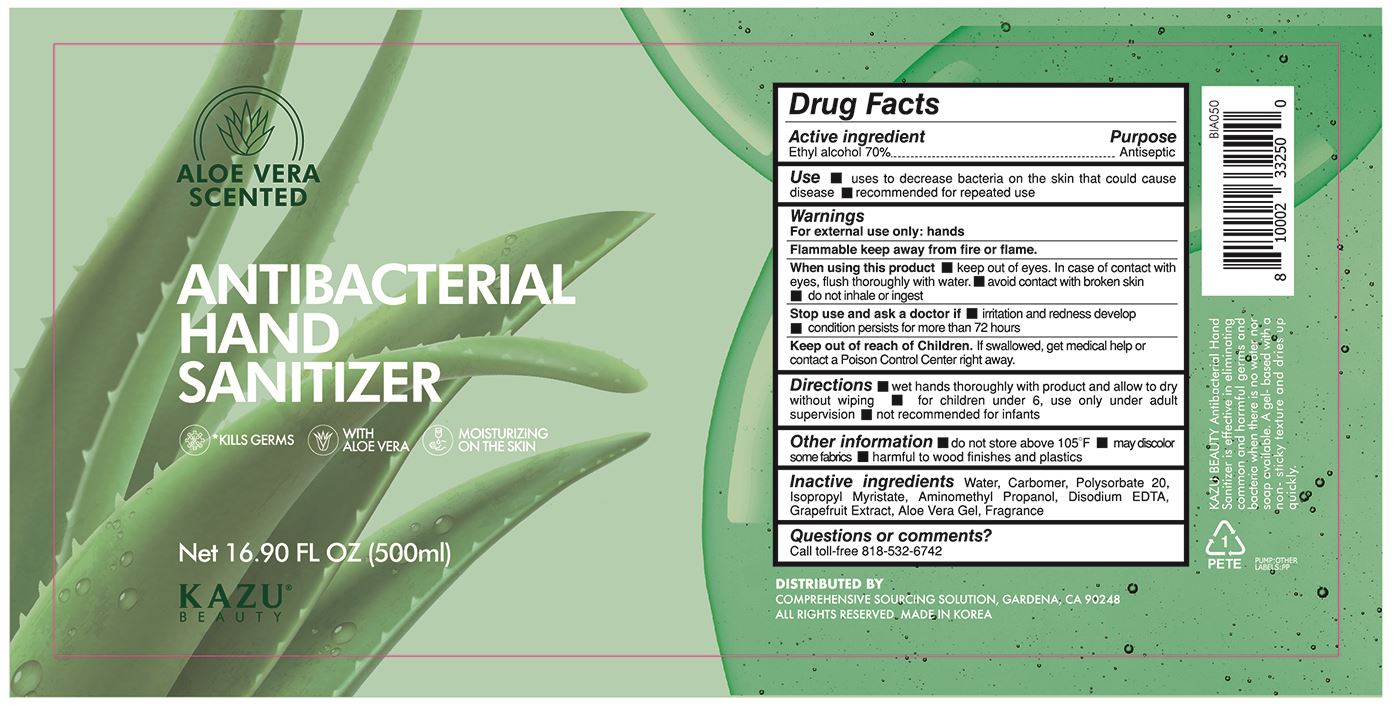 DRUG LABEL: KAZU BEAUTY ANTIBACTERIAL HAND SANITIZER
NDC: 76966-0010 | Form: GEL
Manufacturer: N Bridge Inc.
Category: otc | Type: HUMAN OTC DRUG LABEL
Date: 20200721

ACTIVE INGREDIENTS: ALCOHOL 350 mL/500 mL
INACTIVE INGREDIENTS: ALOE VERA LEAF; GRAPEFRUIT; EDETATE DISODIUM ANHYDROUS; WATER; POLYSORBATE 20; CARBOMER HOMOPOLYMER, UNSPECIFIED TYPE; ISOPROPYL MYRISTATE; AMINOMETHYLPROPANOL

ACTIVE INGREDIENT

Alcohol

INACTIVE INGREDIENT

water, carbomer, polysorbate 20, isopropyl myristate, aminomethyl propanol, disodium edta, grapefruit extract, aloe vera gel

PURPOSE

Antiseptic

keep out of reach of the children

INDICATIONS AND USAGE

wet hands thoroughly with product and allow to dry without wiping

for children under 6, use only under adult supervision

not recommended for infants

WARNINGS

For external use only. Flammable. Keep away from heat or flame.

Do not use

- in children less than 2 months of age
- on open skin wounds

When using this product keep out of eyes, ears, and mouth. In case of contact with eyes, rinse thoroughly with water.

Stop use and ask a doctor if irritation or rash occurs. These may be signs of a serious condition.

Keep out of reach of children. If swallowed, get medical help or contact a Poison Control Center right away.

DOSAGE AND ADMINISTRATION

for external use only